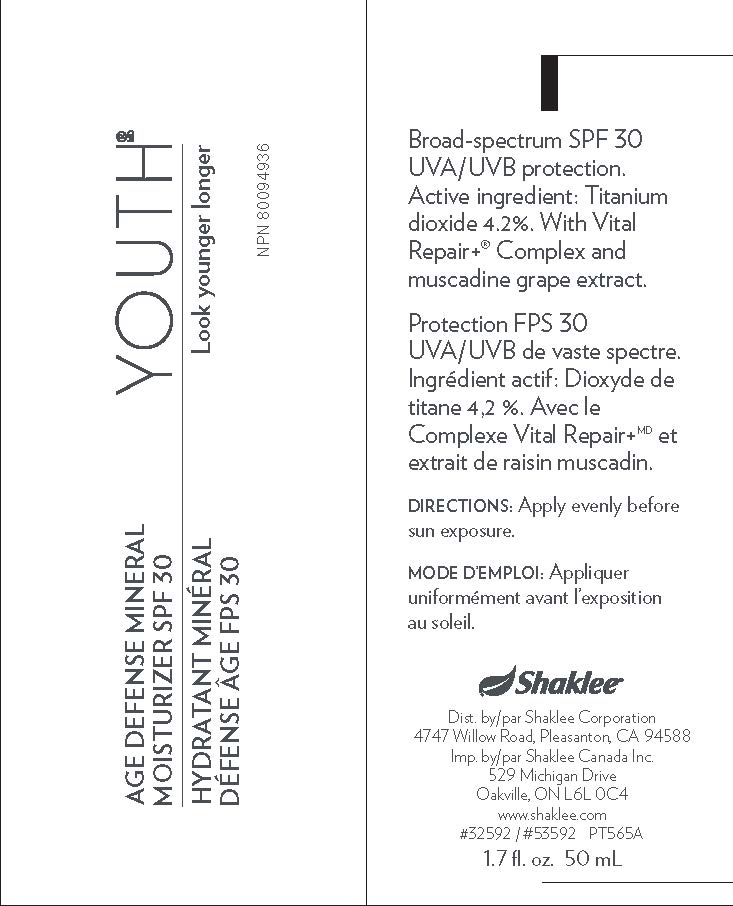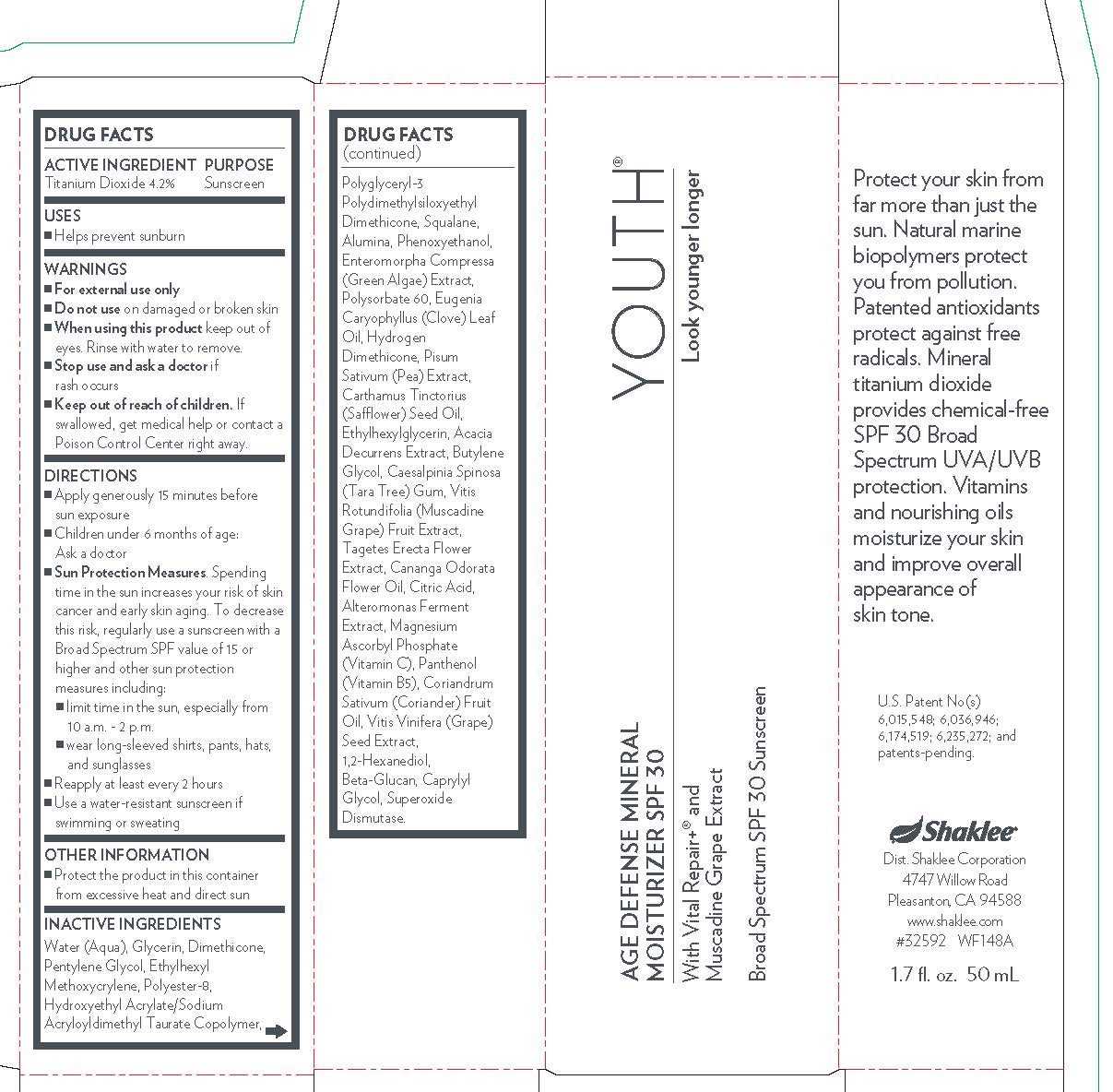 DRUG LABEL: Age Defense Mineral Moisturizer SPF 30
NDC: 59899-051 | Form: LOTION
Manufacturer: Shaklee Corporation
Category: otc | Type: HUMAN OTC DRUG LABEL
Date: 20200601

ACTIVE INGREDIENTS: TITANIUM DIOXIDE 42 mg/1 mL
INACTIVE INGREDIENTS: ALTEROMONAS MACLEODII; POLYGLYCERYL-3 POLYDIMETHYLSILOXYETHYL DIMETHICONE (4000 MPA.S); PEA; MAGNESIUM ASCORBYL PHOSPHATE; PANTHENOL; CORIANDER OIL; CAPRYLYL GLYCOL; SAFFLOWER OIL; ETHYLHEXYLGLYCERIN; ACACIA DECURRENS WHOLE; WATER; ULVA COMPRESSA; SQUALANE; POLYSORBATE 60; DIMETHICONE; ETHYLHEXYL METHOXYCRYLENE; PHENOXYETHANOL; VITIS VINIFERA SEED; 1,2-HEXANEDIOL; GLYCERIN; TAGETES ERECTA FLOWER; CANANGA ODORATA FLOWER; ANHYDROUS CITRIC ACID; ALUMINUM OXIDE; PENTYLENE GLYCOL; POLYESTER-8 (1400 MW, CYANODIPHENYLPROPENOYL CAPPED); CAESALPINIA SPINOSA RESIN; MUSCADINE GRAPE; HYDROXYETHYL ACRYLATE/SODIUM ACRYLOYLDIMETHYL TAURATE COPOLYMER (45000 MPA.S AT 1%); CLOVE LEAF OIL; BUTYLENE GLYCOL; SUPEROXIDE DISMUTASE (SACCHAROMYCES CEREVISIAE); GLUCONOLACTONE; HYDROGEN DIMETHICONE (13 CST)

ACTIVE INGREDIENT

Titanium Dioxide 4.2%

PURPOSE

Sunscreen

INDICATIONS AND USAGE

Helps prevent sunburn

WARNINGS

For external use only

Do not use on damaged or broken skin

When using this product keep out of eyes. Rince with water to remove.

Stop use and ask a doctor if rash occurs

Stop use and ask a doctor if rash occurs

KEEP OUT OF REACH OF CHILDREN

Keep our of reach of children. If swallowed, get medical help or contact a Poison Control Center right away.

Directions

- Apply generously 15 minutes before sun exposure
- Children under 6 months of age: Ask a doctor
- Sun Protection Measures. Spending time in the sun increases your risk of skin cancer and early skin aging. To decrease this risk, regularly use a sunscreen with a Broad Spectrum SPF value of 15 or higher and other sun protection measures including:

1. limit time in the sun, especially from 10 a.m. - 2 p.m.
2. Wear long-sleeved shirts, pants, hats, and sunglasses

- Reapply at least every 2 hours
- Use a water-resistant sunscreen if swimming or sweating

Other Information

- Protect the product in this container from excessive heat and direct sun

INACTIVE INGREDIENT

Water (Aqua), Glyverin, Dimethicone, Pentylene Glycol, Ethylhexyl Methoxycrylene, Polyester-8, Hydroxyethyl Acrylate/Sodium Acryloyldimethyl Taurate Copolymer, Polyclyceryl-3 Polydimethylciloxyethyl Dimethicone, Squalane, Alumina, Phenoxyethanol, Enteromorpha Compressa (Green Algae) Extract, Polysorbate 60, Eugenia Caryophyllus (Clove) Leaf Oil, Hydrogen Dimethicone, Pisum Sativum (Pea) Extract, Carthamus Tinctorius (Safflower) Seed Oil, Ethylhexylglycerin, Acacia Decurrens Extract, Butylene Glycol, Caesalpinia Spinosa (Tara Tree) Gum, Vitis Rotundifolia (muscadine Grape) Fruis Extract, Tagetes Erecta Flower Extract, Cananga Odorata Flower Oil, Citric Acid, Alteromonas Ferment Extract Magnesium Ascorbyl Phosphate (Vitamin C), Panthenol (Vitamin B5), Coriandrum Sativum (Coriander) Fruit Oil, Vitis Vinifera (Grape) Seed Extract, 1,2-Hexanediol, Beta-Glucan, Caprylyl Glycol, Superoxide Dismutase.